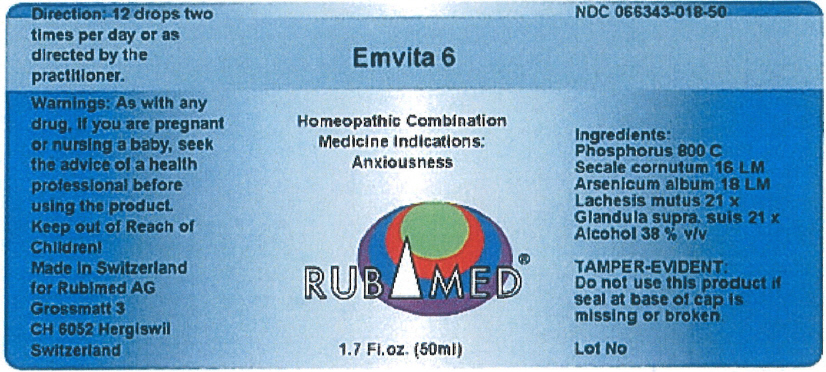 DRUG LABEL: Emvita 6
NDC: 66343-018 | Form: LIQUID
Manufacturer: RUBIMED AG
Category: otc | Type: HUMAN OTC DRUG LABEL
Date: 20150709

ACTIVE INGREDIENTS: PHOSPHORUS 800 [hp_C]/1 mL; CLAVICEPS PURPUREA SCLEROTIUM 16 [hp_M]/1 mL; ARSENIC TRIOXIDE 18 [hp_M]/1 mL; LACHESIS MUTA VENOM 21 [hp_X]/1 mL; SUS SCROFA ADRENAL GLAND 21 [hp_X]/1 mL
INACTIVE INGREDIENTS: Alcohol 0.38 mL/1 mL

Emvita 6

PURPOSE

Homeopathic Combination Medicine Indications: Anxiousness

Ingredients

INACTIVE INGREDIENT

Phosphorus 800 C
Secale cornutum 16 LM
Arsenicum album 18 LM
Lachesis mutus 21 x
Glandula supra. suis 21 x
Alcohol 38 % v/v

TAMPER-EVIDENT

Do not use this product if seal at base of cap is missing or broken.

Direction

12 drops two times per day or as directed by the practitioner.

Warnings

PREGNANCY OR BREAST FEEDING

As with any drug, if you are pregnant or nursing a baby, seek the advice of a health professional before using the product.

Keep out of Reach of Children!

PRINCIPAL DISPLAY PANEL - 50 ml Bottle Label

Emvita 6

Homeopathic Combination
Medicine Indications:
Anxiousness

RUBIMED®

1.7 Fl.oz. (50ml)